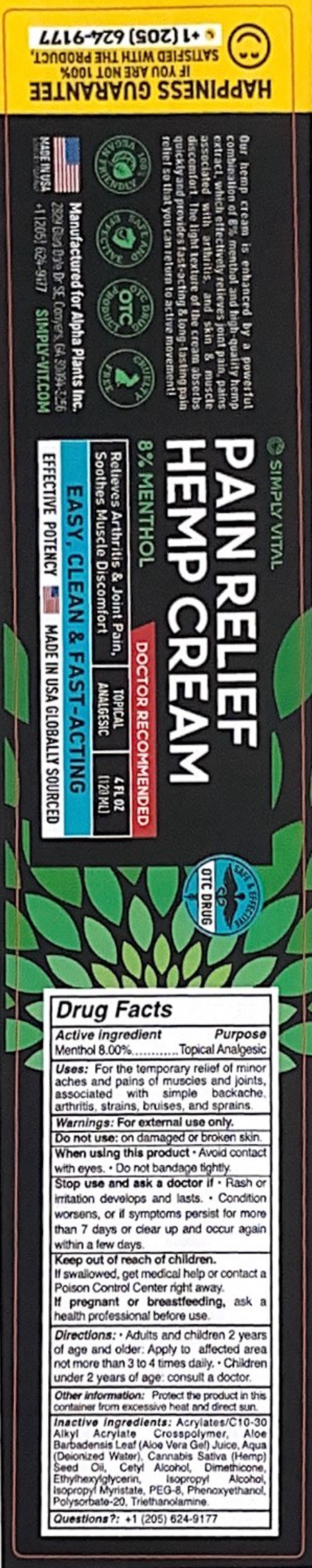 DRUG LABEL: SIMPLY VITAL PAIN RELIEF HEMP
NDC: 82460-345 | Form: CREAM
Manufacturer: ALPHA PLANTS INC
Category: otc | Type: HUMAN OTC DRUG LABEL
Date: 20260119

ACTIVE INGREDIENTS: MENTHOL 80 mg/1 mL
INACTIVE INGREDIENTS: ALOE VERA LEAF; WATER; CANNABIS SATIVA SEED OIL; CETYL ALCOHOL; DIMETHICONE; ETHYLHEXYLGLYCERIN; ISOPROPYL ALCOHOL; ISOPROPYL MYRISTATE; POLYETHYLENE GLYCOL 400; PHENOXYETHANOL; POLYSORBATE 20; TROLAMINE

SIMPLY VITAL PAIN RELIEF HEMP CREAM

Active Ingredient

Menthol 8.00%

Purpose

Topical Analgesic

Uses:

For the temporary relief of minor aches and pains of muscles and joints, associated with simple backache, arthritis, strains, bruises, and sprains

Warnings:

For external use only.

Do not use:

on damaged or brosken skin.

When using this product

- Avoid contact with eyes.
- Do not bandage tightly.

Stop use and ask a doctor if

- Rash or irritation develops and lasts.
- Condition worsens, or if symptoms persist for more than 7 days or clear up and occur again within a few days

Keep out of reach of children.

If swallowed, get medical help or contact a Poison Control Center right away.

If pregnant or breastfeeding,

ask a health professional before use.

Directions:

- Adults and children 2 years of age and older: Apply to affected area not more than 3 to 4 times daily.
- Children under 2 years of age: consult a doctor.

Other information:

Protect the product in this container from excessive heat and direct sun.

Inactive Ingredients:

Acrylates/C10-30 Alkyl Acrylate Crosspolymer, Aloe Barbadensis Leaf (Aloe Vera Gel) Juice, Aqua (Deionized Water), Cannabis Sativa (Hemp) Seed Oil, Cetyl Alcohol, Dimethicone, Ethylhexylglycerin, Isopropyl Alcohol, Isopropyl Myristate, PEG-8, Phenoxyethanol, Polysorbate-20, Triethanolamine.

Questions?:

+1 (205) 624-9177